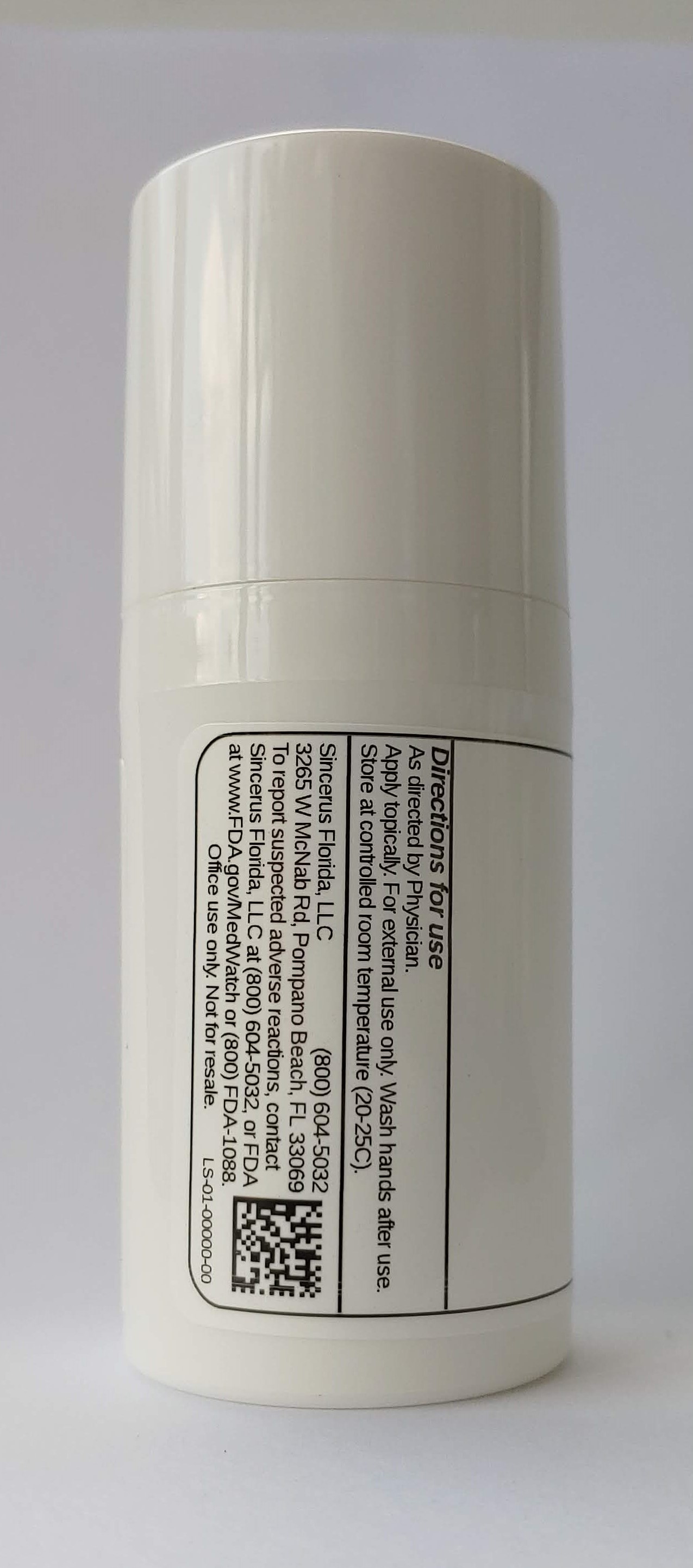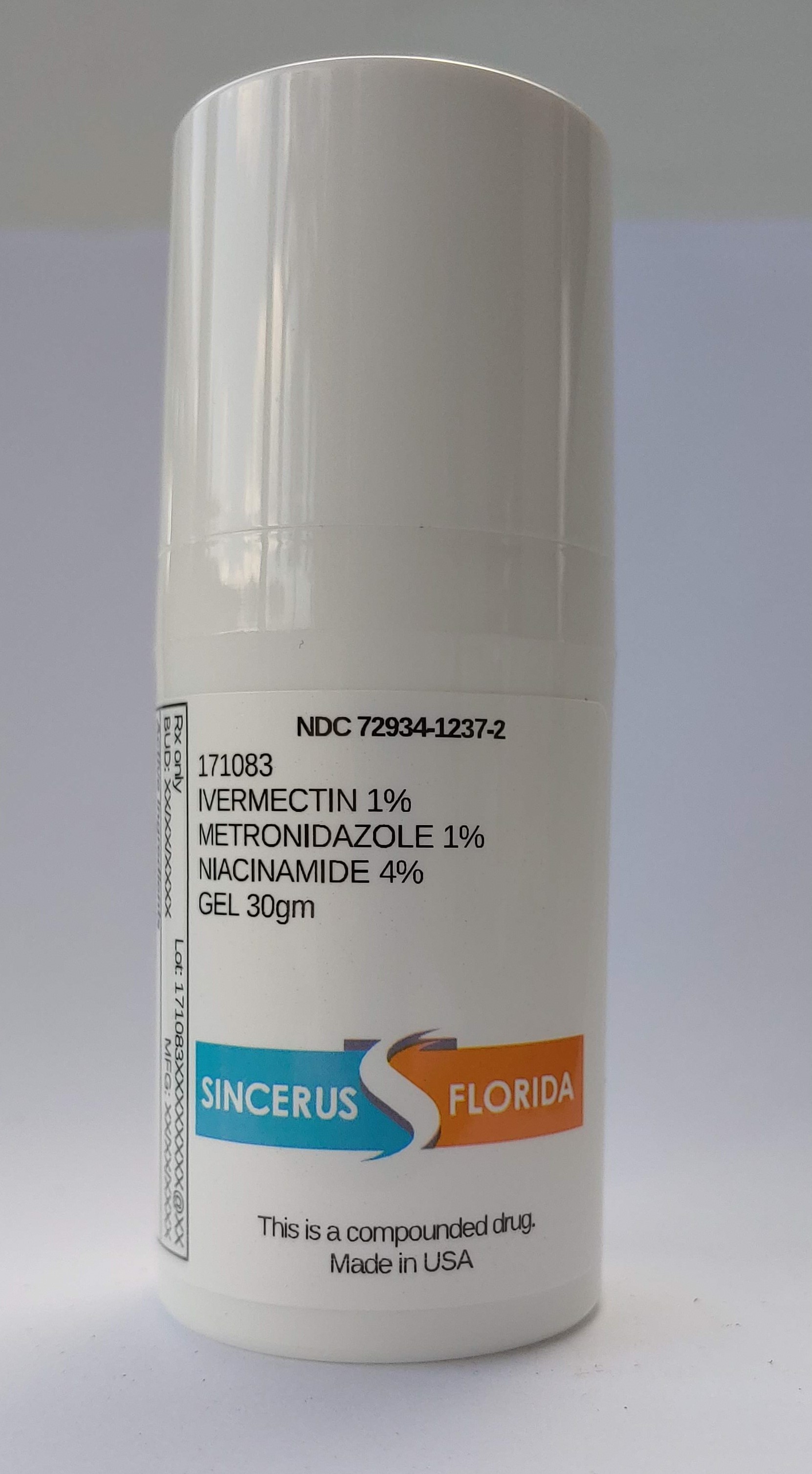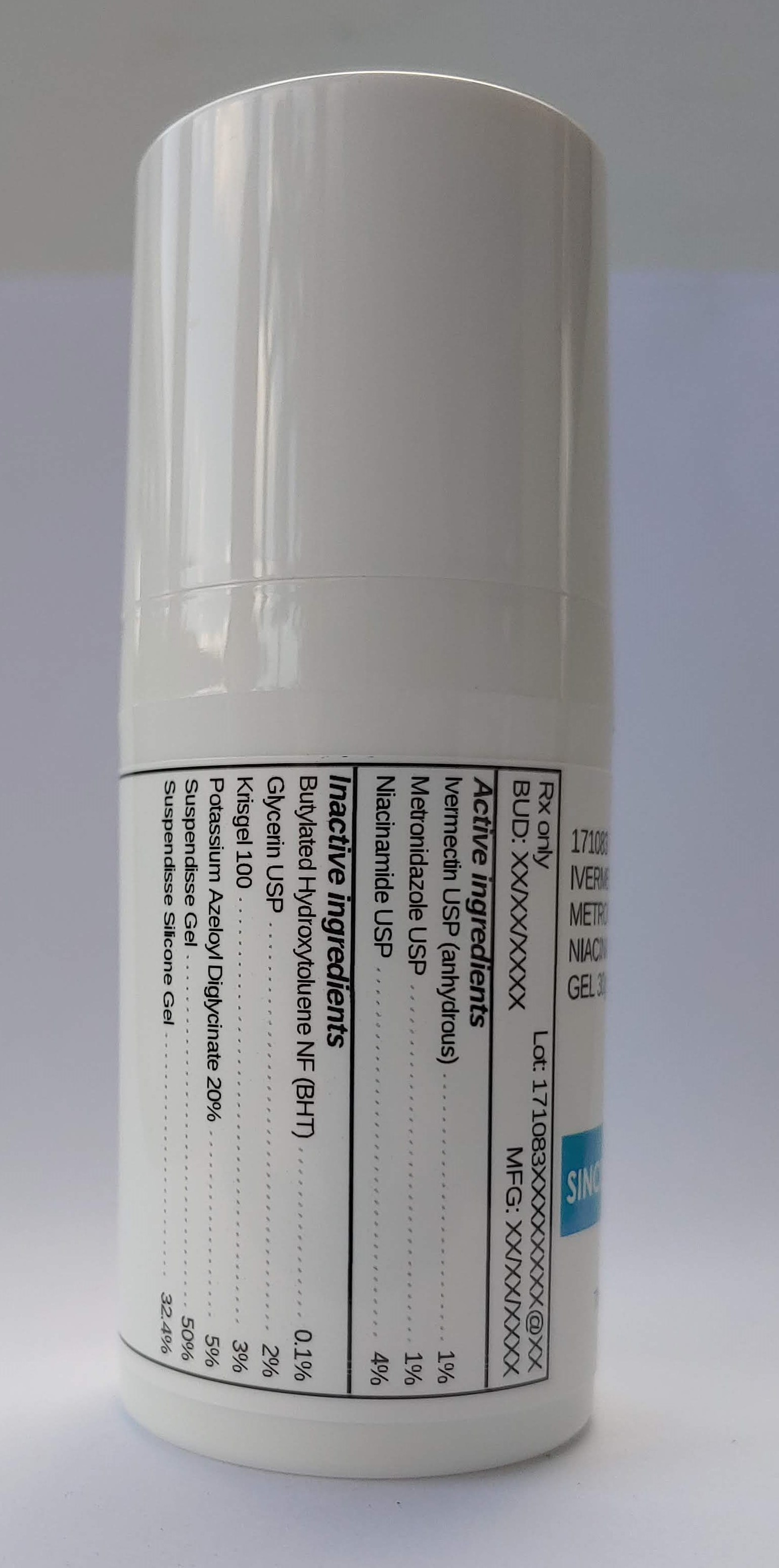 DRUG LABEL: 171083 IVERMECTIN 1% / METRONIDAZOLE 1% / NIACINAMIDE 4%
NDC: 72934-1237 | Form: GEL
Manufacturer: Sincerus Florida, LLC
Category: prescription | Type: HUMAN PRESCRIPTION DRUG LABEL
Date: 20200702

ACTIVE INGREDIENTS: METRONIDAZOLE 1 g/100 g; NIACINAMIDE 4 g/100 g; IVERMECTIN 1 g/100 g

171083 IVERMECTIN 1% / METRONIDAZOLE 1% / NIACINAMIDE 4%